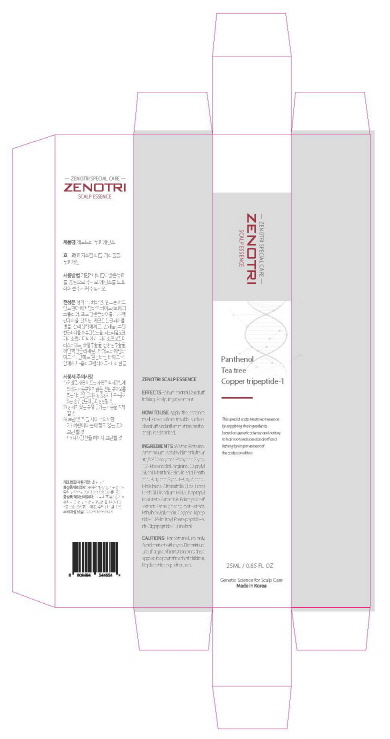 DRUG LABEL: ZENOTRI Scalp Essence
NDC: 81817-101 | Form: GEL
Manufacturer: CHROMACH Co., Ltd.
Category: otc | Type: HUMAN OTC DRUG LABEL
Date: 20210513

ACTIVE INGREDIENTS: SALICYLIC ACID 0.06 g/25 mL
INACTIVE INGREDIENTS: PROPYLENE GLYCOL 0.75 mL/25 mL; ETHYLHEXYLGLYCERIN 0.00007 mL/25 mL; PANTHENOL 0.05 mL/25 mL; TEA TREE OIL 0.01 mL/25 mL; ASIAN GINSENG 0.001 mL/25 mL; PREZATIDE COPPER 0.000001 mL/25 mL; NEPIDERMIN; TERT-BUTYL ALCOHOL 0.01 mL/25 mL; ISOPROPYL MYRISTATE 0.002 mL/25 mL; BETAINE 0.5 mL/25 mL; AMMONIUM ACRYLOYLDIMETHYLTAURATE/VP COPOLYMER 0.22 mL/25 mL; 1,2-HEXANEDIOL 0.13 mL/25 mL; CAPRYLYL GLYCOL 0.08 mL/25 mL; EDETATE DISODIUM ANHYDROUS 0.05 mL/25 mL; BUTYLENE GLYCOL 0.02 mL/25 mL; PALMITOYL PENTAPEPTIDE-4 0.000001 mL/25 mL; MENTHOL 0.08 mL/25 mL; WATER 23.02 mL/25 mL; ARTEMISIA PRINCEPS LEAF 0.001 mL/25 mL; ARGININE 0.03 mL/25 mL

Active Ingredient

Salicylic acid 0.25%

Purpose

Antidandruff

Use

For the relief of the symptoms of dandruff

Warnings

For external use only

When using this product avoid contact with the eyes. If contact occurs, rinse eyes thoroughly with water.

Stop use and ask a doctor if condition worsens or does not improve after regular use of this product as directed

Keep out of reach of children. If swallowed, get medical help or contact a Poison Control Center right away

Directions

For best results use at least twice a week or as directed by a doctor.

Apply the essence to all areas where trouble such as dandruff and inflammation on the scalp is absorbed.

Inactive ingredients

Water, Propylene Glycol, Betaine, Ammonium Acryloyldimethyltaurate/VP Copolymer, 1,2-Hexanediol, Caprylyl Glycol, Menthol, Salicylic acid, Disodium EDTA, Panthenol, Arginine, Butylene Glycol, t-Butyl Alcohol, Melaleuca Alternifolia (Tea Tree) Leaf Oil, Isopropyl Myristate, Artemisia Princeps Leaf Extract, Panax ginseng root Extract, Ethylhexylglycerin, Copper Tripeptide-1, Palmitoyl Pentapeptide-4, rh-Oligopeptide-1